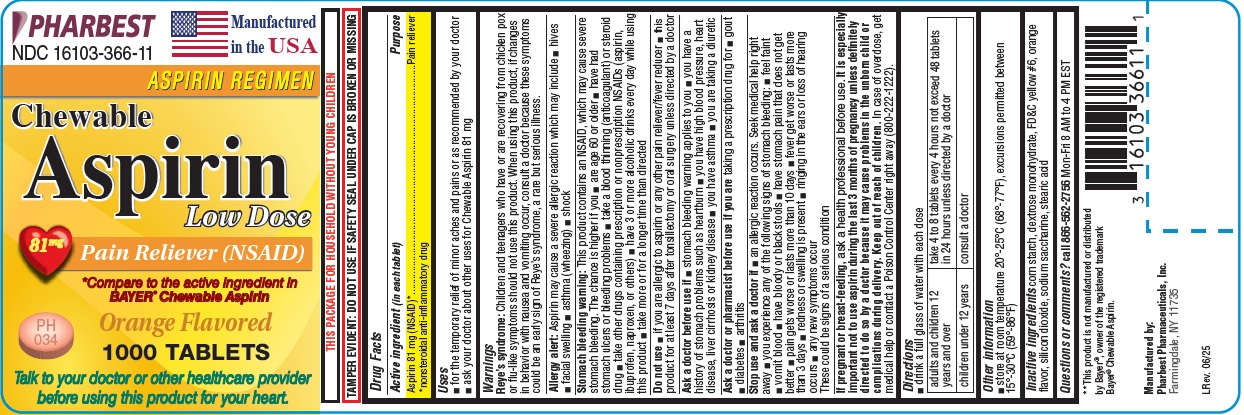 DRUG LABEL: Low Dose Aspirin
NDC: 16103-366 | Form: TABLET, CHEWABLE
Manufacturer: Pharbest Pharmaceuticals, Inc.
Category: otc | Type: HUMAN OTC DRUG LABEL
Date: 20251224

ACTIVE INGREDIENTS: ASPIRIN 81 mg/1 1
INACTIVE INGREDIENTS: STARCH, CORN; DEXTROSE MONOHYDRATE; FD&C YELLOW NO. 6; SILICON DIOXIDE; SACCHARIN SODIUM; STEARIC ACID

Drug Facts

Active Ingredient (in each tablet)

Aspirin 81mg (NSAID)*

*nonsteroidal anti-inflammatory drug

Purpose

Pain reliever

Uses

- for the temporary relief of minor aches and pains or as recommended by your doctor
- ask your doctor about other uses for Chewable Aspirin 81 mg

Warnings

Reye's syndrome: Children and teenagers who have or are recovering from chicken pox or flu-like symptoms should not use this product. When using this product, if changes in behavior with nausea and vomiting occur, consult a doctor because these symptoms could be an early sign of Reye's syndrome, a rare but serious illness.

Allergy alert: Aspirin may cause a severe allergic reaction which may include

- hives
- facial swelling
- asthma (wheezing)
- shock

Stomach bleeding warning: This product contains an NSAID, which may cause severe stomach bleeding.

The chance is higher if you

- are age 60 or older
- have had stomach ulcers or bleeding problems
- take a blood thinning (anticoagulant) or steroid drug
- take other drugs containing prescription or nonprescription NSAIDs (aspirin, ibuprofen, naproxen, or others)
- have 3 or more alcoholic drinks every day while using this product
- take more or for a longer time than directed

Do not use

- if you are allergic to aspirin or any other pain reliever/fever reducer
- this product for at least 7 days after tonsillectomy or oral surgery unless directed by a doctor

Ask a doctor before use if

- the stomach bleeding warning applies to you
- you have a history of stomach problems such as heartburn
- you have high blood pressure, heart disease, liver cirrhosis or kidney disease
- you have asthma
- you are taking a diuretic

Ask a doctor or pharmacist before use if you are

taking a prescription drug for

- gout
- diabetes
- arthritis

Stop use and ask a doctor if

- you experience any of the following signs of stomach bleeding: • feel faint • vomit blood • have bloody or black stools • have stomach pain that does not get better
- an allergic reaction occurs. Seek mredical help right away
- pain gets worse or lasts more than 10 days
- fever gets worse or lasts more than 3 days
- redness or swelling is present
- any new symptoms occur
- ringing in the ears or loss of hearing occurs

These could be signs of a serious condition

If pregnant or breast-feeding,

ask a health professional before use. It is especially important not to use aspirin during the last 3 months of pregnancy unless definitely directed to do so by a doctor because it may cause problems in the unborn child or complications during delivery.

Keep out of reach of children.

In case of overdose, get medical help or contact a Poison Control Center right away (800-222-1222).

Directions

- drink a full glass of water with each dose
- adults and children 12 years and over: take 4 to 8 tablets every 4 hours not to exceed 48 tablets in 24 hours unless directed by a doctor
- children under 12 years: consult a doctor

Other information

- Tamper Evident: Do not use if safety seal under cap is broken or missing
- store at room temperature 20°-25°C (68°-77°F), excursions permitted between 15-30°C(59-86°F)

Inactive ingredients

Corn starch, dextrose monohydrate, FD&C yellow #6, orange flavor, silicon dioxide, sodium saccharine, stearic acid

Questions or comments?

call 866-562-2756 Mon-Fri 8 AM to 4 PM EST

PACKAGE LABEL

PHARBEST

NDC 16103-366-11

Manufactured in the USA

Aspirin Regimen

Chewable

Aspirin

Low Dose

81mg Pain Reliever (NSAID)

*Compare to the active ingredient in BAYER® Chewable Aspirin

Orange Flavored

1000 TABLETS

Talk to your doctor or other healthcare provider before using this product for your heart.